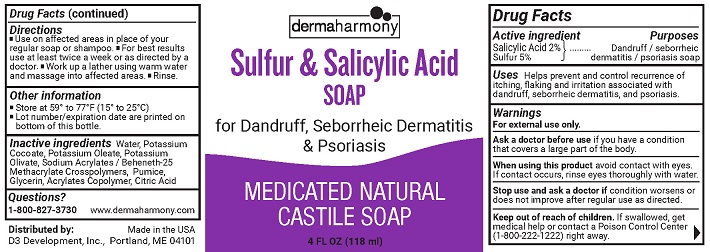 DRUG LABEL: Dermaharmony Sulfur and Salicylic Acid
NDC: 71819-006 | Form: LIQUID
Manufacturer: D3 Development, Inc.
Category: otc | Type: HUMAN OTC DRUG LABEL
Date: 20241220

ACTIVE INGREDIENTS: SULFUR 5 g/100 mL; SALICYLIC ACID 2 g/100 mL
INACTIVE INGREDIENTS: ACRYLIC ACID; CARBOMER HOMOPOLYMER TYPE A (ALLYL PENTAERYTHRITOL CROSSLINKED); CARBOMER HOMOPOLYMER TYPE C (ALLYL PENTAERYTHRITOL CROSSLINKED); PUMICE; WATER; POTASSIUM COCOATE; GLYCERIN; POTASSIUM OLIVATE; POTASSIUM OLEATE; CITRIC ACID MONOHYDRATE

Dermaharmony Sulfur and Salicylic Acid Liquid Soap

Drug Facts

Active ingredient

Salicylic Acid 2%

Sulfur 5%

Purpose

Dandruff / sebhorreic dermatitis / psoriasis soap

Uses

Helps prevent and control recurrence of itching, flaking and irritation associated with dandruff, sebhorreic dermatitis, and psoriasis

Warnings

For external use only.

Ask a doctor before use if you havea condition that covers a large area of the body.

When using this product,avoid contact with eyes. If contact occurs, rinse eyes thoroughly with water.

Stop use and ask a doctor ifcondition worsens or does not improve after regular use as directed.

Keep out of reach of children.If swallowed, get medical help or contact a Poison Control Center (1-800-222-1222) right away.

Directions

- Use on affected areas in place of your regular soap or shampoo.
- For best results use at least twice a week or as directed by a doctor.
- Work up a lather using warm water and massage into affected areas.
- Rinse.

Other information

- Store at 59° to 77°F (15° to 25°C)
- Lot number/expiration date are printed on bottom of this bottle.

Inactive ingredients

Water, Potassium Cocoate, Potassium Oleate, Potassium Olivate, Sodium Acrylates / Beheneth-25 Methacrylate Crosspolymers, Pumice, Glycerin, Acrylates Copolymer, Citric Acid

Questions?

1-800-827-3730

www.dermaharmony.com

Distributed by:

D3 Development, Inc., Portland, ME 04101

Made in the USA

PACKAGE LABEL

dermaharmony

Sulfur & Salicylic Acid SOAP

For Dandruff, Sebhorreic Dermatitis & Psoriasis

MEDICATED NATURAL CASTILE SOAP

4 FL OZ (118 ml)